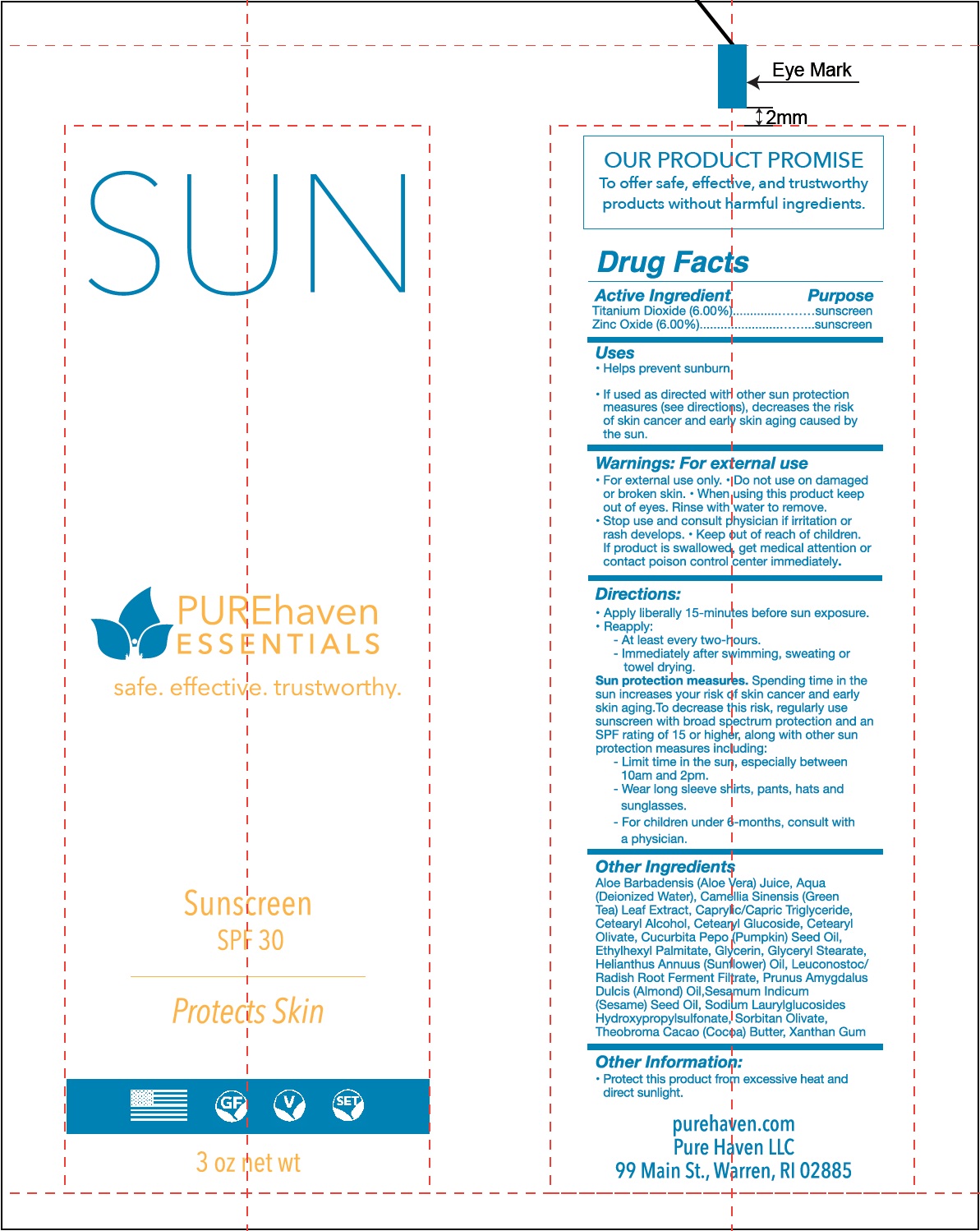 DRUG LABEL: Pure Haven Essentials
NDC: 71355-819 | Form: CREAM
Manufacturer: Pure Haven LLC
Category: otc | Type: HUMAN OTC DRUG LABEL
Date: 20231111

ACTIVE INGREDIENTS: TITANIUM DIOXIDE 60 mg/1 mL; ZINC OXIDE 60 mg/1 mL
INACTIVE INGREDIENTS: ALOE VERA LEAF; WATER; GREEN TEA LEAF; MEDIUM-CHAIN TRIGLYCERIDES; CETOSTEARYL ALCOHOL; CETEARYL GLUCOSIDE; CETEARYL OLIVATE; PUMPKIN SEED OIL; ETHYLHEXYL PALMITATE; GLYCERIN; GLYCERYL MONOSTEARATE; HELIANTHUS ANNUUS FLOWERING TOP; LEUCONOSTOC/RADISH ROOT FERMENT FILTRATE; ALMOND; SESAME OIL; SORBITAN OLIVATE; COCOA; XANTHAN GUM

Pure Haven Essentials SPF-30

Active Ingredient

Titanium Dioxide (6.00%) Zinc Oxide (6.00%)

Purpose

Sunscreen

Uses

- Helps prevent sunburn
- If used as directed with other sun protection measures (see directions), decreases the risk of skin cancer and early skin aging caused by the sun.

Warnings:

For external use

- For external use only.

Do not use

on damaged or broken skin.

When using this product

keep out of eyes. Rinse with water to remove.

Stop use and consult physician

if irritation or rash develops.

Keep out of reach of children.

If product is swallowed, get medical attention or contact poison control center immediately.

Directions:

- Apply liberally 15-minutes before sun exposure.
- Reapply:

- At least every tow-hours.

- Immediately after swimming, sweating or towel drying.

Spending time in the sun increase your risk of skin cancer and early skin aging . To decrease this risk, regularly use sunscreen with broad spectrum protection and an SPF rating of 15 or higher, along with other sun protection measures including: Sun protection measures.

- Limit time in the sun, especially between 10am and 2pm.

- Wear long sleeve shirts, pants, hats and sunglasses.

- For childre under 6-months, consult with a physician.

Other Ingredients

Aloe Barbadensis (Aloe vera) Juice, Aqua (Deionized Water), Camellia Sinensis (Green Tea) Leaf Extract, Caprylic/Capric Triglyceride, Cetearyl Alcohol, Cetearyl Glucoside, Cetearyl Olivate, Cucurbita Pepo (Pumpkin) Seed Oil, Ethylhexyl Palmitate, Glycerin, Glyceryl Stearate, Helianthus Annuus (Sunflower) Oil, Leuconostoc/Radish Root Ferment Filtrate, Prunus Amygdalus Dulcis (Almond) Oil, Sesamum Indicum (Sesame) Seed Oil, Sodium Laurylglucosides Hydroxypropylsulfonate, Sorbitan Olivate, Theobroma Cacao (Cocoa) Butter, Xanthan Gum

Other Information:

- Protect this product from excessive heat and direct sunlight.